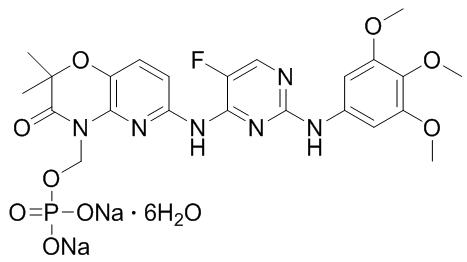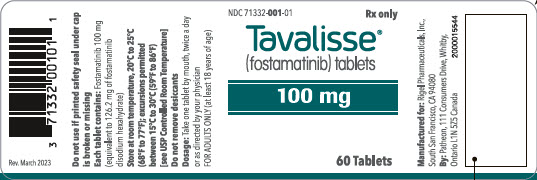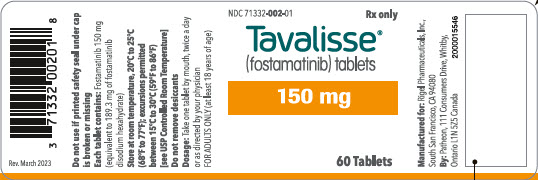 DRUG LABEL: TAVALISSE
NDC: 71332-001 | Form: TABLET
Manufacturer: Rigel Pharmaceuticals, Inc.
Category: prescription | Type: HUMAN PRESCRIPTION DRUG LABEL
Date: 20251105

ACTIVE INGREDIENTS: FOSTAMATINIB 100 mg/1 1
INACTIVE INGREDIENTS: MANNITOL; SODIUM BICARBONATE; SODIUM STARCH GLYCOLATE TYPE A POTATO; POVIDONE, UNSPECIFIED; MAGNESIUM STEARATE; POLYVINYL ALCOHOL, UNSPECIFIED; TITANIUM DIOXIDE; POLYETHYLENE GLYCOL 3350; TALC; FERRIC OXIDE YELLOW; FERRIC OXIDE RED

HIGHLIGHTS OF PRESCRIBING INFORMATION

These highlights do not include all the information needed to use TAVALISSE® safely and effectively. See full prescribing information for TAVALISSE.
TAVALISSE® (fostamatinib disodium hexahydrate) tablets, for oral use
Initial U.S. Approval: 2018

1 INDICATIONS AND USAGE

TAVALISSE is a kinase inhibitor indicated for the treatment of thrombocytopenia in adult patients with chronic immune thrombocytopenia (ITP) who have had an insufficient response to a previous treatment.

2 DOSAGE AND ADMINISTRATION

- Initiate TAVALISSE at 100 mg orally twice daily with or without food. After 4 weeks, increase to 150 mg twice daily, if needed, to achieve platelet counts of at least 50 × 10^9/L as necessary to reduce the risk of bleeding. (2.1)
- Manage adverse reactions using dose reduction, interruption of treatment, or discontinuation. (2.3)
- Discontinue TAVALISSE after 12 weeks of treatment if the platelet count does not increase to a level sufficient to avoid clinically important bleeding. (2.5)

3 DOSAGE FORMS AND STRENGTHS

Tablets: 100 mg, 150 mg (3)

4 CONTRAINDICATIONS

None. (4)

5 WARNINGS AND PRECAUTIONS

- Hypertension: Monitor blood pressure every 2 weeks until stable, then monthly. Manage hypertension using standard antihypertensive treatment and, if needed, interrupt, reduce or discontinue TAVALISSE. (5.1)
- Hepatotoxicity: Monitor LFTs monthly. If LFT levels are elevated, interrupt, reduce or discontinue TAVALISSE. (5.2)
- Diarrhea: Manage diarrhea with supportive measures. If diarrhea becomes severe, interrupt, reduce or discontinue TAVALISSE. (5.3)
- Neutropenia: Monitor ANC monthly, and for infection. If neutrophil count decreases below 1.0 × 10^9/L, interrupt, reduce or discontinue TAVALISSE. (5.4)
- Embryo-Fetal Toxicity: TAVALISSE can cause fetal harm. Advise patients of potential risk to a fetus and to use effective contraception. (5.5)

6 ADVERSE REACTIONS

The most common adverse reactions (≥5% and more than placebo) are diarrhea, hypertension, nausea, respiratory infection, dizziness, ALT/AST increased, rash, abdominal pain, fatigue, chest pain and neutropenia. (6.1)

To report SUSPECTED ADVERSE REACTIONS, contact Rigel Pharmaceuticals, Inc. at 1-800-983-1329 or FDA at 1-800-FDA-1088 or www.fda.gov/medwatch.

7 DRUG INTERACTIONS

- Strong CYP3A4 Inhibitors: Concomitant use with a strong CYP3A4 inhibitor increases exposure to R406 (the major active metabolite).(7)
- Strong CYP3A4 Inducers: Concomitant use is not recommended. (7)

8 USE IN SPECIFIC POPULATIONS

- Pregnancy: Advise women of the risk to a fetus. (8.1)
- Lactation: Advise women not to breastfeed. (8.2)

FULL PRESCRIBING INFORMATION

1 INDICATIONS AND USAGE

TAVALISSE is indicated for the treatment of thrombocytopenia in adult patients with chronic immune thrombocytopenia (ITP) who have had an insufficient response to a previous treatment.

2 DOSAGE AND ADMINISTRATION

2.1 Recommended Dosage

Initiate TAVALISSE at a dose of 100 mg taken orally twice daily. After a month, if platelet count has not increased to at least 50 × 10^9/L, increase TAVALISSE dose to 150 mg twice daily.

Use the lowest dose of TAVALISSE to achieve and maintain a platelet count at least 50 × 10^9/L as necessary to reduce the risk of bleeding.

TAVALISSE may be taken with or without food. In the case of a missed dose of TAVALISSE, instruct patients to take their next dose at its regularly scheduled time.

2.2 Monitoring

After obtaining baseline assessments:

- Monitor CBCs, including platelet counts, monthly until a stable platelet count (at least 50 × 10^9/L) is achieved. Thereafter, continue to monitor CBCs, including neutrophils, regularly.
- Monitor liver function tests (LFTs) (e.g., ALT, AST, and bilirubin) monthly.
- Monitor blood pressure every 2 weeks until establishment of a stable dose, then monthly thereafter.

2.3 Dose Modification for Adverse Reactions

TAVALISSE dose modification is recommended based on individual safety and tolerability. Management of some adverse reactions may require dose-interruption, reduction, or discontinuation.

A dose reduction schedule is provided in Table 1, based on daily dose. For example, if a patient is on the maximum dose at the time of an adverse reaction, the first dose reduction would be from 300 mg/day to 200 mg/day.

Table 1: Dose Reduction Schedule
Daily Dose | Administered as:
Daily Dose | AM | PM
300 mg/day | 150 mg | 150 mg
200 mg/day | 100 mg | 100 mg
150 mg/day | 150 mg [Once daily TAVALISSE should be taken in the morning.] | ---
100 mg/day [If further dose reduction below 100 mg/day is required, discontinue TAVALISSE.] | 100 mg | ---

The recommended dose modifications for adverse reactions are provided in Table 2.

Table 2: Recommended Dose Modifications and Management for Specific Adverse Reactions
Adverse Reaction | Recommended Action
Hypertension
Stage 1: systolic between 130-139 or diastolic between 80-89 mmHg | - Initiate or increase dosage of antihypertensive medication for patients with increased cardiovascular risk, and adjust as needed until BP is controlled. - If the BP target is not met after 8 weeks, reduce TAVALISSE to next lower daily dose (refer to Table 1).
Stage 2: systolic at least 140 or diastolic at least 90 mmHg | - Initiate or increase dosage of antihypertensive medication, and adjust as needed until BP is controlled. - If BP remains 140/90 mmHg or higher for more than 8 weeks, reduce TAVALISSE to next lower daily dose (refer to Table 1). - If BP remains 160/100 mmHg or higher for more than 4 weeks despite aggressive antihypertensive therapy, interrupt or discontinue TAVALISSE.
Hypertensive crisis: systolic over 180 and/or diastolic over 120 mmHg | - Interrupt or discontinue TAVALISSE. - Initiate or increase dosage of antihypertensive medication, and adjust as needed until BP is controlled. If BP returns to less than the target BP, resume TAVALISSE at same daily dose. - If repeat BP is 160/100 mmHg or higher for more than 4 weeks despite aggressive antihypertensive treatment, discontinue TAVALISSE.
Hepatotoxicity
AST/ALT is 3 × ULN or higher and less than 5 × ULN | If patient is symptomatic (e.g., nausea, vomiting, abdominal pain):; - Interrupt TAVALISSE. - Recheck LFTs every 72 hours until ALT/AST values are no longer elevated (below 1.5 × ULN) and total BL remains less than 2 × ULN. - Resume TAVALISSE at next lower daily dose (refer to Table 1).
AST/ALT is 3 × ULN or higher and less than 5 × ULN | If patient is asymptomatic:; - Recheck LFTs every 72 hours until ALT/AST are below 1.5 × ULN) and total BL remains less than 2 × ULN. - Consider interruption or dose reduction of TAVALISSE if ALT/AST and TBL remain in this category (AST/ALT is 3 to 5 × ULN; and total BL remains less than 2 × ULN) - If interrupted, resume TAVALISSE at next lower daily dose (refer to Table 1) when ALT/AST are no longer elevated (below 1.5 × ULN) and total BL remains less than 2 × ULN.
AST/ALT is 5 × ULN or higher and total BL is less than 2 × ULN | - Interrupt TAVALISSE. - Recheck LFTs every 72 hours: - If AST and ALT decrease, recheck until ALT and AST are no longer elevated (below 1.5 × ULN) and total BL remains less than 2 × ULN; resume TAVALISSE at next lower daily dose (refer to Table 1). - If AST/ALT persist at 5 × ULN or higher for 2 weeks or more, discontinue TAVALISSE.
AST/ALT is 3 × ULN or higher and total BL is greater than 2 × ULN | - Discontinue TAVALISSE.
Elevated unconjugated (indirect) BL in absence of other LFT abnormalities | - Continue TAVALISSE with frequent monitoring since isolated increase in unconjugated (indirect) BL may be due to UGT1A1 inhibition
Diarrhea
Diarrhea | - Manage diarrhea using supportive measures (e.g., dietary changes, hydration and/or antidiarrheal medication) early after the onset until symptom(s) have resolved. - If symptom(s) become severe (Grade 3 or above), temporarily interrupt TAVALISSE. - If diarrhea improves to mild (Grade 1), resume TAVALISSE at the next lower daily dose (refer to Table 1).
Neutropenia
Neutropenia | - If absolute neutrophil count decreases (ANC less than 1.0 × 10^9/L) and remains low after 72 hours, temporarily interrupt TAVALISSE until resolved (ANC greater than 1.5 × 10^9/L). - Resume TAVALISSE at the next lower daily dose (refer to Table 1).
ALT = alanine aminotransferase; AST = aspartate aminotransferase; BP = blood pressure; BL = bilirubin; ULN = upper limit of normal; LFT = liver function tests (AST, ALT, total BL with fractionation if elevated, alkaline phosphatase); AST/ALT = AST or ALT

2.4 Dose Modification for Drug Interactions

Concomitant use with a strong CYP3A4 inhibitor increases exposure to R406 (the major active metabolite). Monitor for toxicities of TAVALISSE that may require TAVALISSE dose modifications (see Table 1) when given concurrently with a strong CYP3A4 inhibitor [see Drug Interactions (7.1)].

2.5 Discontinuation

Discontinue TAVALISSE after 12 weeks of treatment if the platelet count does not increase to a level sufficient to avoid clinically important bleeding [see Clinical Studies (14)].

3 DOSAGE FORMS AND STRENGTHS

TAVALISSE is available as:

- 100 mg tablet: orange, film-coated, round, biconvex tablets debossed with "100" on one side and "R" on the reverse side.
- 150 mg tablet: orange, film-coated, oval, biconvex tablets debossed with "150" on one side and "R" on the reverse side.

4 CONTRAINDICATIONS

None.

5 WARNINGS AND PRECAUTIONS

5.1 Hypertension

Hypertension can occur with TAVALISSE treatment; hypertensive crisis occurred in 1% of patients. Patients with pre-existing hypertension may be more susceptible to the hypertensive effects of TAVALISSE.

Monitor blood pressure every 2 weeks until stable, then monthly and adjust or initiate antihypertensive therapy to ensure maintenance of blood pressure control during TAVALISSE therapy. If increased blood pressure persists despite appropriate therapy, TAVALISSE interruption, reduction or discontinuation may be necessary [see Dosage and Administration (2.3)].

5.2 Hepatotoxicity

Elevated liver function tests (LFTs), mainly ALT and AST, can occur with TAVALISSE.

In the placebo-controlled studies, laboratory testing showed maximum ALT/AST levels more than 3 × the upper limit of normal (ULN) in 9% of patients receiving TAVALISSE [see Adverse Reactions (6.1)]. For most patients, transaminases recovered to baseline levels within 2 to 6 weeks of dose-modification.

Monitor liver function tests monthly during treatment. If ALT or AST increase more than 3 × ULN, manage hepatotoxicity using TAVALISSE interruption, reduction, or discontinuation [see Dosage and Administration (2.3)].

5.3 Diarrhea

Diarrhea occurred in 31% of patients treated with TAVALISSE. Severe diarrhea occurred in 1% of patients treated with TAVALISSE. Monitor patients for the development of diarrhea. Manage diarrhea using supportive care measures, including dietary changes, hydration and/or antidiarrheal medication, early after the onset of symptoms. Interrupt, dose reduce, or discontinue TAVALISSE if diarrhea becomes severe (Grade 3 or above) [see Dosage and Administration (2.3)].

5.4 Neutropenia

Neutropenia occurred in 6% of patients treated with TAVALISSE; febrile neutropenia occurred in 1% of patients.

Monitor the ANC monthly, and for infection during treatment. Manage toxicity with TAVALISSE interruption, reduction or discontinuation [see Dosage and Administration (2.3)].

5.5 Embryo-Fetal Toxicity

Based on findings from animal studies and its mechanism of action, TAVALISSE can cause fetal harm when administered to a pregnant woman. In animal reproduction studies, administration of fostamatinib to pregnant rats and rabbits during organogenesis caused adverse developmental outcomes including embryo-fetal mortality (post-implantation loss), alterations to growth (lower fetal weights), and structural abnormalities (variations and malformations) at maternal exposures (AUCs) approximately 0.3 and 10 times the human exposure at the maximum recommended human dose (MRHD), respectively. Advise pregnant women of the potential risk to a fetus. Advise females of reproductive potential to use effective contraception during treatment and for at least 1 month after the last dose. [see Use in Specific Populations (8.1) and Clinical Pharmacology (12.1)].

6 ADVERSE REACTIONS

The following clinically important adverse reactions, that can become serious are described elsewhere in the labeling:

- Hypertension [see Warnings and Precautions (5.1)]
- Hepatotoxicity [see Warnings and Precautions (5.2)]
- Diarrhea [see Warnings and Precautions (5.3)]
- Neutropenia [see Warnings and Precautions (5.4)]

6.1 Clinical Trials Experience

Because clinical trials are conducted under widely varying conditions, adverse reaction rates observed in the clinical trials of a drug cannot be directly compared to rates in the clinical trials of another drug and may not reflect the rates observed in practice.

TAVALISSE was studied in two randomized, double-blind, placebo-controlled trials that were identical in design. The data described below reflect exposure to TAVALISSE in 102 patients with chronic ITP who had received one or more prior ITP treatment(s). Groups were stratified with respect to splenectomy and severity of thrombocytopenia. Patients randomized to the TAVALISSE arm received 100 mg orally twice daily. Based upon platelet count and tolerability, if a patient's platelet count did not increase to at least 50 × 10^9/L, the TAVALISSE dose could be increased to 150 mg twice daily after one month. In the placebo controlled studies, the median duration of TAVALISSE exposure in these studies was 86 days (range 8 to 183) [see Clinical Studies (14) for additional details for patients on TAVALISSE].

In the ITP double-blind studies, serious adverse drug reactions were febrile neutropenia, diarrhea, pneumonia, and hypertensive crisis, which each occurred in 1% of patients receiving TAVALISSE. In addition, severe adverse reactions observed in patients receiving TAVALISSE included dyspnea and hypertension (both 2%); and neutropenia, arthralgia, chest pain, diarrhea, dizziness, nephrolithiasis, pain in extremity, toothache, syncope and hypoxia (all 1%) [see Warnings and Precautions (5.1)]. Table 3 presents the common adverse reactions from these studies.

Table 3: Incidence of Common (≥ 5%) Adverse Reactions from Double-Blind Clinical Studies (FIT 1 and FIT 2)
Adverse Reaction | TAVALISSE (N=102) |  |  |  | Placebo (N=48)
Adverse Reaction | Mild % | Moderate % | Severe % | TOTAL % | Mild % | Moderate % | Severe % | TOTAL %
Diarrhea [Includes diarrhea and frequent bowel movement.] | 21 | 10 | 1 | 31 | 13 | 2 | 0 | 15
Hypertension [Includes hypertension, blood pressure (BP) increased, BP diastolic abnormal, and BP diastolic increased.] | 17 | 9 | 2 | 28 | 10 | 0 | 2 | 13
Nausea | 16 | 3 | 0 | 19 | 8 | 0 | 0 | 8
Dizziness | 8 | 2 | 1 | 11 | 6 | 2 | 0 | 8
ALT increased | 5 | 6 | 0 | 11 | 0 | 0 | 0 | 0
AST increased | 5 | 4 | 0 | 9 | 0 | 0 | 0 | 0
Respiratory infection [Includes upper respiratory tract infection, respiratory tract infection, lower respiratory tract infection, and viral upper respiratory tract infection.] | 7 | 4 | 0 | 11 | 6 | 0 | 0 | 6
Rash [Includes rash, rash erythematous and rash macular.] | 8 | 1 | 0 | 9 | 2 | 0 | 0 | 2
Abdominal pain [Includes abdominal pain, and abdominal pain upper.] | 5 | 1 | 0 | 6 | 2 | 0 | 0 | 2
Fatigue | 4 | 2 | 0 | 6 | 0 | 2 | 0 | 2
Chest pain | 2 | 3 | 1 | 6 | 2 | 0 | 0 | 2
Neutropenia [Includes neutropenia and neutrophil count decreased.] | 3 | 2 | 1 | 6 | 0 | 0 | 0 | 0
ALT = Alanine aminotransferase
AST = Aspartate aminotransferase
Note: Common adverse reactions defined as all adverse reactions occurring at a rate of ≥ 5% of patients in the TAVALISSE group and greater than placebo rate.

Table 4: Elevations in Hepatic Transaminases During Placebo-Controlled Clinical Studies
Enzyme | Maximum Level of Elevation | Number of Patients (%)
Enzyme | Maximum Level of Elevation | TAVALISSE (N=102) | Placebo (N=48)
Alanine aminotransferase (ALT) and/or Aspartate aminotransferase (AST) | >3 and ≤5 × ULN | 3 (3) | 0
Alanine aminotransferase (ALT) and/or Aspartate aminotransferase (AST) | >5 and ≤10 × ULN | 5 (5) | 0
Alanine aminotransferase (ALT) and/or Aspartate aminotransferase (AST) | ≥10 × ULN | 1 (1) | 0

7 DRUG INTERACTIONS

7.1 Effect of Other Drugs on TAVALISSE

Strong CYP3A4 Inhibitors

Concomitant use with strong CYP3A4 inhibitors increases exposure to R406 (the major active metabolite), which may increase the risk of adverse reactions. Monitor for toxicities of TAVALISSE that may require dose reduction (see Table 1) when given concurrently with a strong CYP3A4 inhibitor [see Dosage and Administration (2.4) and Clinical Pharmacology (12.3)].

Strong CYP3A4 Inducers

Concomitant use with a strong CYP3A4 inducer reduces exposure to R406. Concomitant use of TAVALISSE with strong CYP3A4 inducers is not recommended [see Clinical Pharmacology (12.3)].

7.2 Effect of TAVALISSE on Other Drugs

CYP3A4 Substrates

Concomitant use of TAVALISSE may increase concentrations of some CYP3A4 substrate drugs. Monitor for toxicities of CYP3A4 substrate drug that may require dosage reduction when given concurrently with TAVALISSE [see Clinical Pharmacology (12.3)].

BCRP Substrates

Concomitant use of TAVALISSE may increase concentrations of BCRP substrate drugs (e.g., rosuvastatin). Monitor for toxicities of BCRP substrate drug that may require dosage reduction when given concurrently with TAVALISSE [see Clinical Pharmacology (12.3)].

P-Glycoprotein (P-gp) Substrates

Concomitant use of TAVALISSE may increase concentrations of P-gp substrates (e.g., digoxin). Monitor for toxicities of the P-gp substrate drug that may require dosage reduction when given concurrently with TAVALISSE [see Clinical Pharmacology (12.3)].

8 USE IN SPECIFIC POPULATIONS

8.1 Pregnancy

Risk Summary

Based on findings from animal studies and the mechanism of action, TAVALISSE can cause fetal harm when administered to a pregnant woman [see Clinical Pharmacology (12.1)].

There are no available data in pregnant women to inform the drug-associated risk. In animal reproduction studies, administration of fostamatinib to pregnant rats and rabbits during organogenesis caused adverse developmental outcomes that were directly attributed to exposure in utero to the major fostamatinib metabolite (R406) at maternal exposures (AUC) as low as 0.3 and 10 times the exposure in patients at the maximum recommended human dose (MRHD), respectively (see Data). Advise pregnant women of the potential risk to a fetus.

All pregnancies have a background risk of birth defect, loss, or other adverse outcomes. In the U.S. general population, the estimated background risk of major birth defects and miscarriage in clinically recognized pregnancies is 2-4% and 15-20%, respectively. An estimated background risk of major birth defects and miscarriage for the chronic ITP population is 8% and 4-11%, respectively.

Data

Animal Data

In a fertility and early embryonic development study in female rats, fostamatinib was administered orally for 15 days before mating to Day 7 of pregnancy, which caused a slight decrease in pregnancy rates and an increase in post-implantation loss were seen at maternal doses approximately 4.2 times the dose in patients at the MRHD.

In embryo-fetal development studies, pregnant animals were orally administered fostamatinib during the period of organogenesis at doses up to 25 and 50 mg/kg/day in rats and rabbits, respectively. The adverse developmental outcomes included an increase in embryo-fetal mortality (post-implantation loss), alterations to growth (lower fetal weights), and structural abnormalities (variations and malformations). These effects occurred at maternal exposures (AUCs) of 3,763 ng.h/mL in rats and 111,105 ng.h/mL in rabbits that were approximately 0.3 and 10 times the human exposure at the MRHD in rats and rabbits, respectively.

In a peri and postnatal development study in rats, fostamatinib was orally administered at doses of 2.5, 12.5, and 25 mg/kg/day from gestation day 7 until lactation day 20. The dose of 25 mg/kg/day was associated with maternal toxicity, including decreased body weights, body weight gains, and food consumption. At doses as low as 12.5 mg/kg/day fostamatinib caused increases in newborn mortality (neonatal mortality), alterations in growth and/or development (lower neonatal weights into post-weaning and structural abnormalities [malformations]). Functional impairment (delayed sexual maturation) was observed at 25 mg/kg/day. There was no evidence of neurobehavioral defects (maze learning and shuttle box avoidance) or immunological compromise (influenza host resistance challenge) in the F1 generation or latent untoward effects in the F2 generation. The maternal doses were approximately 2.1 and 4.2 times the MHRD in patients.

8.2 Lactation

Risk Summary

There are no data on the presence of fostamatinib and/or its metabolites in human milk, the effects on the breastfed child, or on milk production. In rodents, R406 (the major active metabolite) was detected in maternal milk in concentrations 5- to 10-fold higher than in maternal plasma. Because of the potential for serious adverse reactions in a breastfed child from TAVALISSE, advise a lactating woman not to breastfeed during treatment with TAVALISSE and for at least 1 month after the last dose.

8.3 Females and Males of Reproductive Potential

Pregnancy Testing

Based on animal studies, TAVALISSE can cause fetal harm when administered to a pregnant woman [see Use in Specific Populations (8.1)]. For females of reproductive potential, verify pregnancy status prior to initiating TAVALISSE.

Contraception

Females

Based on animal studies, TAVALISSE can cause fetal harm when administered to a pregnant woman [see Use in Specific Populations (8.1)]. Advise females of reproductive potential to use effective contraception during treatment with TAVALISSE and for at least 1 month after the last dose.

Infertility

There are no data on the effect of TAVALISSE on human fertility. Based on the finding of reduced pregnancy rates in animal studies, TAVALISSE may affect female fertility [see Use in Specific Populations (8.1)].

8.4 Pediatric Use

Safety and effectiveness in pediatric patients have not been established. TAVALISSE is not recommended for use in patients less than 18 years of age because adverse effects on actively growing bones were observed in nonclinical studies. In subchronic, chronic, and carcinogenicity studies of TAVALISSE, chondrodystrophy of the femoral head was seen in rodents. In a study in juvenile rabbits, growth plate dysplasia was observed in the proximal femur and femoro-tibial joint, and bone marrow cellularity was reduced in the femur and sternum.

8.5 Geriatric Use

Of the 102 patients with ITP who received TAVALISSE, 28 (27%) were 65 years of age and older, while 11 (11%) were 75 years of age and older. In patients 65 years of age and older, 6 (21%) patients experienced serious adverse events and 5 (18%) experienced adverse events leading to treatment withdrawal while in patients under 65 years of age, 7 (9%) and 5 (7%) experienced serious adverse events and adverse events leading to treatment withdrawal, respectively. In patients 65 years of age and older who received TAVALISSE, 11 (39%) patients experienced hypertension versus 2 (18%) placebo compared to 17 (23%) in patients under 65 of age versus 4 (11%) placebo. No overall differences in effectiveness were observed in these patients compared to younger patients.

10 OVERDOSAGE

There is no specific antidote for overdose with TAVALISSE, and the amount of R406 (the pharmacologically active metabolite of fostamatinib) cleared by dialysis is negligible. In the event of an overdose, monitor patient closely for signs and symptoms of adverse reactions, and treat the reactions with supportive care [see Warnings and Precautions (5)].

11 DESCRIPTION

Fostamatinib is a tyrosine kinase inhibitor. TAVALISSE is formulated with the disodium hexahydrate salt of fostamatinib, a phosphate prodrug that converts to its pharmacologically active metabolite, R406, in vivo.

The chemical name for fostamatinib disodium hexahydrate is disodium (6-[[5-fluoro-2-(3,4,5-trimethoxyanilino) pyrimidin-4-yl]amino]-2,2-dimethyl-3-oxo-pyrido[3,2-b][1,4]oxazin-4-yl)methyl phosphate hexahydrate. The molecular formula is C23H24FN6Na2O9P∙6H2O, and the molecular weight is 732.52. The structural formula is:

Fostamatinib disodium is a white to off-white powder that is practically insoluble in pH 1.2 aqueous buffer, slightly soluble in water, and soluble in methanol.

Each TAVALISSE oral tablet contains 100 mg or 150 mg fostamatinib, equivalent to 126.2 mg or 189.3 mg fostamatinib disodium hexahydrate, respectively.

The inactive ingredients in the tablet core are mannitol, sodium bicarbonate, sodium starch glycolate, povidone, and magnesium stearate. The inactive ingredients in the film coating are polyvinyl alcohol, titanium dioxide, polyethylene glycol 3350, talc, iron oxide yellow, and iron oxide red.

12 CLINICAL PHARMACOLOGY

12.1 Mechanism of Action

Fostamatinib is a tyrosine kinase inhibitor with demonstrated activity against spleen tyrosine kinase (SYK). The major metabolite of fostamatinib, R406, inhibits signal transduction of Fc-activating receptors and B-cell receptor. The fostamatinib metabolite R406 reduces antibody-mediated destruction of platelets.

12.2 Pharmacodynamics

Mean treatment-related increases of 2.93 mmHg in systolic blood pressure and 3.53 mmHg in diastolic blood pressure over placebo were observed following TAVALISSE doses of 100 mg twice daily for 28 days. About 31% of patients in the TAVALISSE group experienced blood pressures ≥140/90 mmHg compared to 15% of patients in the placebo group. Blood pressure returned to baseline within 1 week following TAVALISSE discontinuation in 58% (11 of 19) of patients in the TAVALISSE group who had blood pressures ≥140/90 mmHg.

Cardiac Electrophysiology

At 2 times the maximum recommended dose, TAVALISSE did not prolong the QT interval to a clinically relevant extent.

12.3 Pharmacokinetics

TAVALISSE is a prodrug that is converted in the gut to the major active metabolite, R406. Mean (± standard deviation [SD]) exposure estimates of R406 are 550 (± 270) ng/mL for Cmax and 7080 (± 2670) ng∙h/mL for AUC. R406 exposure is approximately dose proportional up to 200 mg twice daily (1.3 times the 150 mg dosage). R406 accumulates approximately 2- to 3-fold upon twice daily dosing at 100–160 mg (0.67 to 1.06 times the 150 mg dosage).

Absorption

After oral administration of TAVALISSE, the absolute bioavailability of R406 was 55%. The median tmax of R406 is approximately 1.5 hours (range: 1 to 4 hours). Negligible levels of fostamatinib were found in plasma.

Effect of Food

Administration of TAVALISSE with a high-calorie, high-fat meal (deriving approximately 150, 250, and 500–600 calories from protein, carbohydrate, and fat, respectively) increased R406 AUC by 23% and Cmax by 15% [see Dosage and Administration (2.1)].

Distribution

In in vitro studies, the R406 is 98.3% protein bound in human plasma. The red blood cell to plasma concentration ratio is approximately 2.6. The mean (± SD) volume of distribution at steady-state of R406 is 256 (± 92) L.

Elimination

The mean (± SD) terminal half-life of R406 is approximately 15 (± 4.3) hours.

Metabolism

TAVALISSE is metabolized in the gut by alkaline phosphatase to the major active metabolite, R406. R406 is extensively metabolized, primarily through pathways of CYP450-mediated oxidation (by CYP3A4) and glucuronidation (by UDP glucuronosyltransferase [UGT]1A9). R406 is the predominant moiety in the systemic circulation, and there was minimal exposure to any R406 metabolites.

Excretion

Following an oral dose of TAVALISSE, approximately 80% of the R406 metabolite is excreted in feces with approximately 20% excreted in the urine. The major component excreted in urine was R406 N-glucuronide. The major components excreted in feces were R406, O-desmethyl R406 and a metabolite produced by gut bacteria from the O-desmethyl metabolite of R406.

Specific Populations

Population pharmacokinetics analyses indicate TAVALISSE is not altered based on age, sex, race/ethnicity. In addition, the pharmacokinetics of TAVALISSE is not altered in patients with renal impairment (creatinine clearance [CLcr] ≥ 30 to < 50 mL/min, estimated by Cockcroft Gault equation and end stage renal disease requiring dialysis), or hepatic impairment (Child-Pugh Class A, B and C).

Drug Interaction Studies

Clinical Pharmacology Studies

No significant interactions were seen with concomitant use of TAVALISSE with the following drugs: methotrexate (OAT1/3 transporters), midazolam (CYP3A4 substrate), microgynon (ethinyl estradiol and levonorgestrel), warfarin, pioglitazone (CYP2C8 substrate) and ranitidine (H2-antagonist that increases gastric pH).

Effect of Other Drugs on TAVALISSE

Strong CYP3A4 inhibitor: Concomitant use of ketoconazole (200 mg twice daily for 3.5 days) with a single dose of 80 mg TAVALISSE (0.53 times the 150 mg dosage) increased R406 AUC by 102% and Cmax by 37%.

Moderate CYP3A4 Inhibitor: Concomitant use of verapamil (80 mg three times daily for 4 days) with a single dose of 150 mg TAVALISSE increased R406 AUC by 39% and Cmax by 6% .

CYP3A4 inducer: Concomitant use of rifampicin (600 mg once daily for 8 days) with a single dose of 150 mg TAVALISSE decreased R406 AUC by 75% and Cmax by 59% .

Effect of TAVALISSE on Other Drugs

CYP3A4 substrate: Concomitant use of simvastatin (single dose 40 mg) with 100 mg twice daily TAVALISSE increased simvastatin AUC by 64% and Cmax by 113% and simvastatin acid AUC by 64% and Cmax by 83%.

BCRP substrate: Concomitant use of rosuvastatin (single dose 20 mg) with 100 mg twice daily TAVALISSE increased rosuvastatin AUC by 95% and Cmax by 88%.

P-gp substrate: Concomitant use of digoxin (0.25 mg once daily) with 100 mg twice daily TAVALISSE increased digoxin AUC by 37% and Cmax by 70% .

In Vitro Studies

TAVALISSE is an inhibitor of the human P-gp efflux transporter in vitro.

CYP3A4 and UGT1A9 are involved in the metabolism of R406. R406 is a substrate of P-gp but not of other major transporters (OAT1/3, OCT2, OATP1B1/3, MRP2, and BCRP). R406 can inhibit CYP3A4 and BCRP, and can induce CYP2C8 activity.

R406 is an inhibitor of UGT1A1. Inhibition of UGT1A1 may result in increased unconjugated bilirubin in the absence of other LFT abnormalities.

13 NONCLINICAL TOXICOLOGY

13.1 Carcinogenesis, Mutagenesis, Impairment of Fertility

Fostamatinib was not carcinogenic in a 2-year study in mice when administered daily by oral gavage at doses up to 500/250 mg/kg/day, and was not carcinogenic in rats when administered by oral gavage at 45 mg/kg/day.

Fostamatinib and its major active metabolite (R406) were not mutagenic in an in vitro bacterial reverse mutation (Ames) assay or clastogenic in an in vitro human lymphocyte chromosomal aberration assay or an in vivo mouse bone marrow micronucleus assay.

In a fertility study with oral fostamatinib, all mating (e.g., time to mating, breeding proficiency), sperm assessments (e.g., number and motility), and organ weight (e.g., paired testis weight) parameters in male rats were unaffected by dosages as high as 40 mg/kg/day, which is 6.7 times the MRHD. All mating and fertility parameters in female rats were unaffected by dosages as high as 11 mg/kg/day (which is 1.8 times the MRHD), but a slight decrease in pregnancy rates and an increase in post-implantation loss were seen at 25 mg/kg/day, which is 4.2 times the MRHD.

14 CLINICAL STUDIES

TAVALISSE was studied in two placebo-controlled efficacy and safety studies (referred to as FIT-1 [NCT02076399] and FIT-2 [NCT02076412]), and in an open-label extension study referred to as FIT-3 (NCT 02077192).

Randomized, Placebo-Controlled Studies

A total of 150 patients with persistent or chronic ITP, who had an insufficient response to previous treatment (which included corticosteroids, immunoglobulins, splenectomy, and/or a thrombopoietin receptor agonists) were enrolled in two identical, double-blind, placebo-controlled studies that were conducted in different countries. For each study, patients were randomized 2:1 to TAVALISSE or placebo for 24 weeks; randomization was stratified with respect to prior splenectomy and severity of thrombocytopenia. Stable concurrent ITP therapy (glucocorticoids [< 20 mg prednisone equivalent per day], azathioprine, or danazol) was allowed, and rescue therapy was permitted, if needed. All patients initially received study drug at 100 mg twice daily (or matching placebo). Based on platelet count and tolerability, dose escalation to 150 mg twice daily (or matching placebo) was undertaken in 88% of patients at Week 4 or later. Patients who did not respond to treatment after 12 weeks, as well as patients who completed the 24-week double blind study, were eligible to enroll in open-label extension study (FIT-3).

Patients enrolled in the placebo-controlled studies had a median age of 54 years (range: 20 to 88), and the majority were female (61%) and were White (93%). Prior ITP treatments were varied, with the most common including corticosteroids (94%), immunoglobulins (53%), and thrombopoietin receptor agonists (TPO-RA) (48%). Most patients had chronic ITP (93%), with a median time since ITP diagnosis of 8.45 years, and 35% had undergone splenectomy. At baseline, the median platelet count was 16 × 10^9/L (with almost half [45]%) less than 15 × 10^9/L) and 47% were on stable ITP therapy.

In Study FIT-1, 76 patients were randomized; 51 to the TAVALISSE group and 25 to the placebo group. In Study FIT-2, 74 patients were randomized; 50 to the TAVALISSE group and 24 to the placebo group. The efficacy of TAVALISSE was based on stable platelet response (at least 50 ×10^9/L on at least 4 of the 6 visits between Weeks 14 to 24). Study outcomes for FIT-1 and FIT-2 are shown in Table 5.

Table 5: Study Outcomes from Placebo-Controlled Clinical Studies
Study Outcomes | Study FIT-1 |  | Study FIT-2
Study Outcomes | TAVALISSE (N=51) | Placebo (N=25) | TAVALISSE (N=50) | Placebo (N=24)
Study Outcomes | n (%) | n (%) | n (%) | n (%)
Stable platelet response [Includes all patients with platelet counts and excludes patients whose platelet counts were measured following rescue therapy after Week 10] , [Stable platelet response was prospectively defined as a platelet count of at least 50 × 10^9/L on at least 4 of the 6 visits between Weeks 14 and 24] | 9 (18) | 0 (0) | 8 (16) | 1 (4)
Stable platelet response [Includes all patients with platelet counts and excludes patients whose platelet counts were measured following rescue therapy after Week 10] , [Stable platelet response was prospectively defined as a platelet count of at least 50 × 10^9/L on at least 4 of the 6 visits between Weeks 14 and 24] | p [p-value from Fisher Exact test] = 0.03 |  | NS
Rolled-over into FIT-3 at Week 12 [Patients who did not respond to treatment after 12 weeks were eligible to enroll in open-label extension study.] | 28 (55) | 22 (88) | 33 (66) | 19 (79)
Completed study (Week 24) | 12 (24) | 1 (4) | 13 (26) | 2 (8)
NS = Did not demonstrate a stastistically significant difference between treatment arms

In the FIT-1 and FIT-2 studies a total of 47 patients in the TAVALISSE arm had received a prior TPO-RA treatment; among these patients, 8 patients (17%) achieved a stable response to TAVALISSE. All 8 patients had previously discontinued TPO-RA due to loss of effect. Rescue medication was required by 30% and 45% of patients receiving TAVALISSE or placebo, respectively.

During the placebo-controlled studies, the incidence of bleeding occurred in 29% and 37% of patients in the TAVALISSE and placebo arms, respectively. Moderate, severe and serious bleeding events are described in Table 6. All severe events led to hospitalizations.

Table 6: Incidence of Moderate, Severe and Serious Bleeding-Related Events (Placebo-Controlled Efficacy Population)
Parameter | TAVALISSE Total N=101 n (%) | Placebo Total N=49 n (%)
Incidence of moderate bleeding-related adverse events | 9 (9) | 5 (10)
Incidence of severe bleeding-related adverse events | 1 (1) | 3 (6)
Incidence of serious bleeding-related adverse events | 4 (4) | 5 (10)

Extension Study

The FIT-3 trial is an open label extension study. Patients from FIT-1 and FIT-2 who completed 24 weeks of treatment, or who did not respond to treatment any time after 12 weeks, were eligible to enroll in this study. Patients remained blinded to their treatment assignment from the previous study (TAVALISSE or placebo), so their starting dose in this study was based on their final platelet count. Patients designated as responders (defined as achievement of platelet count of at least 50 × 10^9/L) at the time of roll over continued in the extension study at their current trial dose and regimen. Patients who entered the extension study as non-responders (defined as platelet count less than 50 × 10^9/L) received TAVALISSE 100 mg twice daily regardless of their dose and regimen in the prior study.

For the FIT-3 trial, 123 patients were enrolled, 44 patients previously randomized to placebo and 79 patients previously randomized to TAVALISSE. Stable response in this study was prospectively defined as no 2 visits, at least 4 weeks apart, with a platelet count less than 50 × 10^9/L, without an intervening visit with a platelet count of at least 50 × 10^9/L (unrelated to rescue therapy), within a period of 12 weeks following initial achievement of the target platelet count. Sixty-one of the 123 subjects (50%) have discontinued from the study early.

In a prospectively defined analysis, the 44 subjects treated with placebo in the prior study were evaluated for stable response for TAVALISSE. Ten of these subjects (23%) (including a single subject who was classified as a placebo responder in the prior study) met the criteria for stable response.

Among the subjects who achieved stable response in FIT-1, FIT-2 and FIT-3 trials, 18 subjects maintained the platelet count of at least 50 × 10^9/L for 12 months or longer.

16 HOW SUPPLIED/STORAGE AND HANDLING

TAVALISSE 100 mg tablets are round, biconvex, orange, film-coated tablets debossed with "100" on one side and "R" on the reverse side.

TAVALISSE 150 mg tablets are oval, biconvex, orange, film-coated tablets debossed with "150" on one side and "R" on the reverse side.

100 mg tablets: Available in bottle of 60 with 2 desiccant canisters | NDC 71332-001-01
150 mg tablets: Available in bottle of 60 with 2 desiccant canisters | NDC 71332-002-01

STORAGE AND HANDLING

Store at room temperature, 20°C to 25°C (68°F to 77°F); excursions permitted between 15°C to 30°C (59°F to 86°F) [see USP Controlled Room Temperature]. Do not remove desiccants.

17 PATIENT COUNSELING INFORMATION

Advise the patient to read the FDA-approved patient labeling (Patient Information).

- Hypertension:
  Inform patients that periodic monitoring of their blood pressure is required, as high blood pressure has occurred in patients taking TAVALISSE. Inform patients of the signs and symptoms of hypertension. Advise patients to undergo routine blood pressure monitoring and to contact their health care provider if blood pressure is elevated or if they experience signs or symptoms of hypertension [see Warnings and Precautions (5.1)].
- Hepatotoxicity:
  Inform patients that periodic monitoring of their liver enzymes is required, and any elevations (which may indicate liver injury) will be managed appropriately, including interruption, reduction, or discontinuation of TAVALISSE [see Warnings and Precautions (5.2)].
- Diarrhea:
  Advise patients to use supportive care measures, and if diarrhea becomes severe, it may necessitate interruption, reduction, or discontinuation of TAVALISSE [see Warnings and Precautions (5.3)].
- Neutropenia:
  Inform patients that monitoring of their complete blood counts is required, and a decrease in neutrophils may necessitate interruption, reduction, or discontinuation of TAVALISSE [see Warnings and Precautions (5.4)].
- Advise patients to inform their healthcare providers of all their medications, including prescription medicines, over-the-counter drugs, vitamins, and herbal products [see Drug Interactions (7)].
- Embryo-Fetal Toxicity
  Advise females to inform their healthcare provider if they are pregnant or become pregnant. Inform female patients of the potential risk to a fetus [see Use in Specific Populations (8.1)].
  Advise females of reproductive potential to use effective contraception during treatment and for at least 1 month after receiving the last dose of TAVALISSE [see Warnings and Precautions (5.5) and Use in Specific Populations (8.1, 8.3)].
- Lactation
  Advise lactating women not to breastfeed during treatment with TAVALISSE and for at least 1 month after the last dose [see Use in Specific Populations (8.2)].
- Inform patients that TAVALISSE may be taken with or without food. In the case of a missed dose of TAVALISSE, instruct patients to take their next dose at its regularly scheduled time.

Manufactured for:
Rigel Pharmaceuticals, Inc.
South San Francisco, CA 94080 USA

Manufactured by:
Patheon, Inc.
Whitby, Ontario L1N 5Z5 Canada

PATIENT INFORMATION
TAVALISSE® (TAV-a-leese)
(fostamatinib disodium hexahydrate)
tablets

What is the most important information I should know about TAVALISSE?
TAVALISSE can cause serious side effects, including:

- High blood pressure (hypertension). New or worsening high blood pressure is common in people treated with TAVALISSE and can be severe. Your healthcare provider will check your blood pressure regularly during treatment with TAVALISSE. If needed, your healthcare provider may start you on blood pressure medicine or change your current medicine to treat your blood pressure. Tell your healthcare provider if you get headaches, confusion, dizziness, chest pain or shortness of breath.
- Liver problems. Changes in liver function blood tests are common with TAVALISSE. Liver problems may occur and can be severe. Your healthcare provider will regularly do blood tests to check how well your liver is working during treatment with TAVALISSE.
- Diarrhea. Diarrhea is common in people treated with TAVALISSE and can be severe. Tell your healthcare provider if you get diarrhea during treatment with TAVALISSE. Your healthcare provider may recommend changes in your diet, drinking more water, or medicine to limit these symptoms.
- Decrease in white blood cell counts (neutropenia). Decreases in your white blood cell count are common with TAVALISSE and can be severe. This may increase your risk for infection, including serious infections. Your healthcare provider will regularly do blood tests to check your white blood cell counts.

Your healthcare provider may change your dose, temporarily stop, or permanently stop treatment with TAVALISSE if you have side effects.
See "What are the possible side effects of TAVALISSE?" for more information about side effects.

What is TAVALISSE?
TAVALISSE is a prescription medicine that is used to treat adults with low platelet counts due to chronic immune thrombocytopenia (ITP) when a prior treatment for ITP has not worked well enough.
It is not known if TAVALISSE is safe and effective in children.

Before you take TAVALISSE, tell your healthcare provider about all of your medical conditions, including if you:

- have high blood pressure
- have liver problems
- are pregnant or plan to become pregnant. TAVALISSE can harm your unborn baby.
  - Your healthcare provider will check if you are pregnant before starting treatment with TAVALISSE.
  - Females who can become pregnant should use effective birth control during treatment with TAVALISSE and for at least 1 month after the last dose.
- are breastfeeding or plan to breastfeed. You should not breastfeed during treatment with TAVALISSE and for at least 1 month after the last dose.

Tell your healthcare provider about all the medicines you take, including prescription and over-the-counter medicines, vitamins, and herbal supplements. Taking TAVALISSE with certain other medicines may affect how the other medicines work and other medicines may affect how TAVALISSE works.
Know the medicines you take. Keep a list of them and show it to your healthcare provider and pharmacist when you get a new medicine.

How should I take TAVALISSE?

- Take TAVALISSE exactly as your healthcare provider tells you to take it.
- Take TAVALISSE with or without food.
- If you miss a dose of TAVALISSE, take your next dose at its regularly scheduled time.
- If you take too much TAVALISSE, call your healthcare provider right away or go to the nearest hospital emergency room right away.
- Your healthcare provider will check your platelet count during your treatment with TAVALISSE and may change your dose of TAVALISSE as needed.

What are the possible side effects of TAVALISSE?
See "What is the most important information I should know about TAVALISSE?"
The most common side effects of TAVALISSE include:

- nausea
- dizziness
- respiratory infection

- rash
- tiredness
- chest pain
- stomach (abdomen) pain

These are not all the side effects of TAVALISSE. For more information, ask your healthcare provider or pharmacist.
Call your doctor for medical advice about side effects. You may report side effects to FDA at 1-800-FDA-1088.

How should I store TAVALISSE?

- Store TAVALISSE at room temperature between 68°F and 77°F (20°C to 25°C).
- The bottle of TAVALISSE contains 2 desiccant canisters that help keep your medicine dry. Do not remove the desiccant canisters from the bottle.

Keep TAVALISSE and all medicines out of the reach of children.

General information about the safe and effective use of TAVALISSE
Medicines are sometimes prescribed for purposes other than those listed in the Patient Information. Do not use TAVALISSE for a condition for which it was not prescribed. Do not give TAVALISSE to other people, even if they have the same symptoms that you have. It may harm them. You can ask your healthcare provider or pharmacist for information about TAVALISSE that is written for health professionals.

What are the ingredients in TAVALISSE?
Active ingredient: fostamatinib disodium hexahydrate
Inactive ingredients: The tablet core contains mannitol, sodium bicarbonate, sodium starch glycolate, povidone, and magnesium stearate. The film coating contains polyvinyl alcohol, titanium dioxide, polyethylene glycol 3350, talc, iron oxide yellow, and iron oxide red.
Manufactured for: Rigel Pharmaceuticals, Inc., South San Francisco, CA 94080 USA
Manufactured by: Patheon, Inc., 111 Consumers Drive, Whitby, Ontario L1N 5Z5 Canada
© Rigel Pharmaceuticals, Inc. All rights reserved. TAVALISSE is a registered trademark of Rigel Pharmaceuticals, Inc.
For more information go to www.TAVALISSE.com or call 1-800-983-1329.

This Patient Information has been approved by the U.S. Food and Drug Administration.

Issued: November 2020

PRINCIPAL DISPLAY PANEL - 100 mg Tablet Bottle Label

NDC 71332-001-01
Rx only

Tavalisse®
(fostamatinib) tablets

100 mg

60 Tablets

PRINCIPAL DISPLAY PANEL - 150 mg Tablet Bottle Label

NDC 71332-002-01
Rx only

Tavalisse®
(fostamatinib) tablets

150 mg

60 Tablets